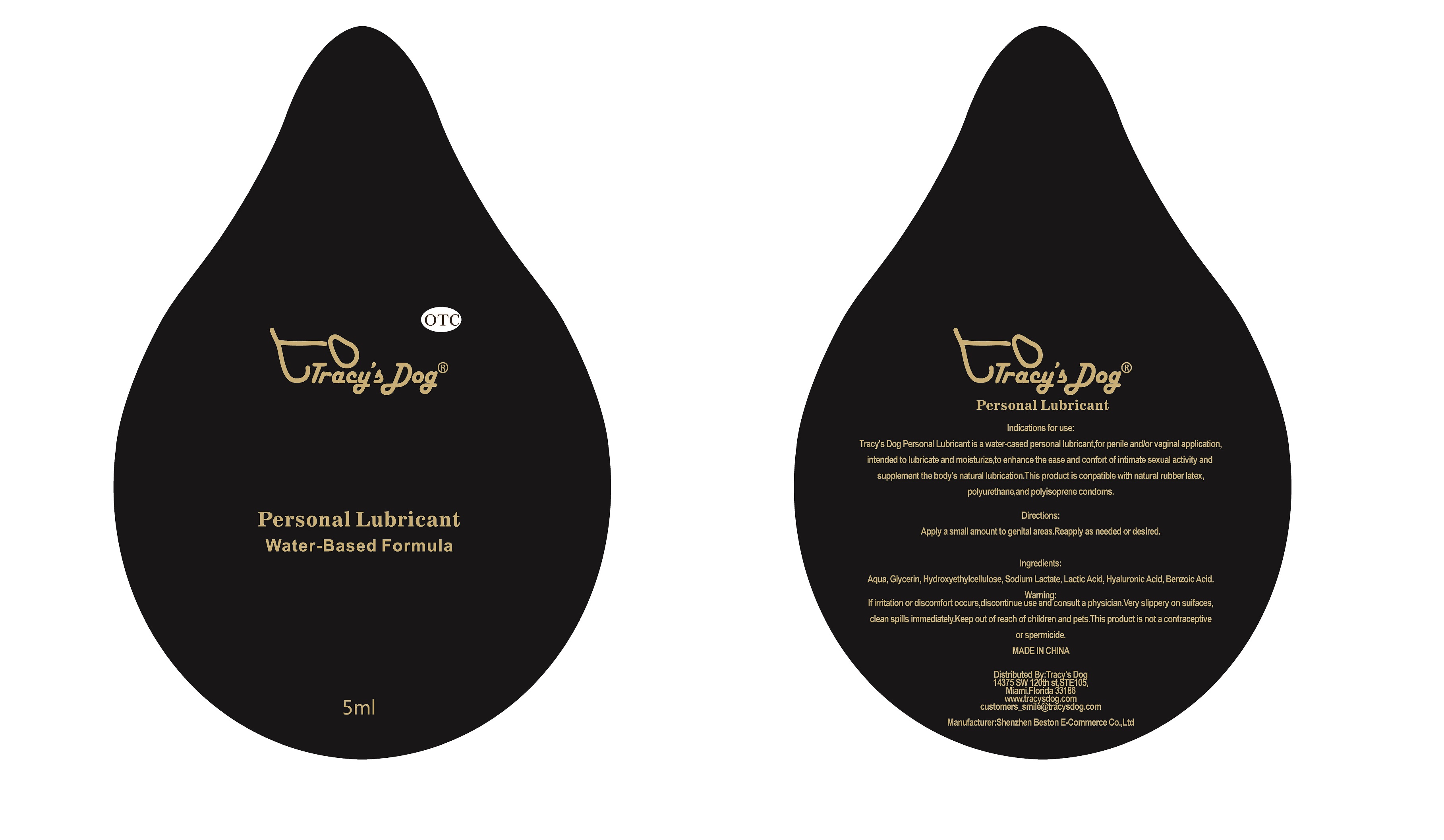 DRUG LABEL: Tracys Dog Personal Lubricant
NDC: 71352-0310 | Form: OIL
Manufacturer: Shenzhen Beston E-Commerce Co., Ltd.
Category: otc | Type: HUMAN OTC DRUG LABEL
Date: 20181205

ACTIVE INGREDIENTS: GLYCERIN 1 g/5 mL
INACTIVE INGREDIENTS: HYDROXYETHYL CELLULOSE (1500 MPA.S AT 1%) 0.08 mL/5 mL; WATER 3.876 mL/5 mL; SODIUM LACTATE 0.015 mL/5 mL; HYALURONIC ACID 0.015 mL/5 mL; BENZOIC ACID 0.004 mL/5 mL; LACTIC ACID, DL- 0.01 mL/5 mL

Tracy's Dog Personal Lubricant, 5mL

Active ingredient

Glycerin

Inactive ingredient

Benzoic Acid

Hyaluronic Acid

Lactic Acid

Sodium Lactate

Hydroxyethyl cellulose

Water

Purpose

This product is a water-based personal lubricant, for penile and/or vaginal application, intended to lubricate and moisturize, to enhance the ease and comfort of intimate sexual activity and supplement to the body's natural lubricant.

When using

Intimate sexual activity.

Do not use

Wound or skin infection.

Stop use

If irritation or discomfort occurs, discontinue the use and consult a physician.
Very slippery on surfaces, clean spills immediately.

Ask doctor

If irritation or discomfort occurs, discontinue the use and consult a physician.

Ask doctor/pharmacist when you current use other drugs.

Keep out of reach of children and pets.

Questions

Please contact us when you have any questions.

Pregnancy or breast feeding

Pregnant or breast feeding women shall follow doctor advice.

Indications & usage

This product is a water-based personal lubricant, for penile and/or vaginal application, intended to lubricate and moisturize, to enhance the ease and comfort of intimate sexual activity and supplement to the body's natural lubricant.

Apply a small amount to genital areas. Reapply as needed or desired.

Dosage & administration

One bottle of 5mL in one package.

Dosage forms & strengths

The lubricant is like oil form.

Active ingredient 1g in this package.

Warnings

If irritation or discomfort occurs, discontinue the use and consult a physician.
Very slippery on surfaces, clean spills immediately.
This product is not a contraceptive or spermicide.

Package label. Principal display panel

-------

Package and Container_5mL

-------